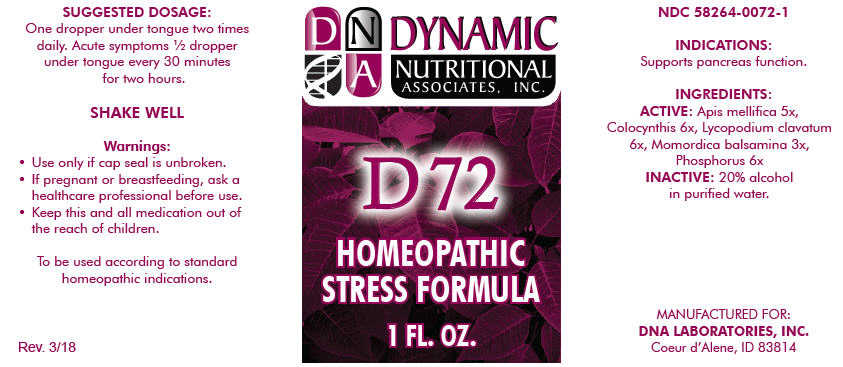 DRUG LABEL: D-72
NDC: 58264-0072 | Form: SOLUTION
Manufacturer: DNA Labs, Inc.
Category: homeopathic | Type: HUMAN OTC DRUG LABEL
Date: 20250113

ACTIVE INGREDIENTS: APIS MELLIFERA 5 [hp_X]/1 mL; CITRULLUS COLOCYNTHIS FRUIT PULP 6 [hp_X]/1 mL; LYCOPODIUM CLAVATUM SPORE 6 [hp_X]/1 mL; MOMORDICA BALSAMINA IMMATURE FRUIT 3 [hp_X]/1 mL; PHOSPHORUS 6 [hp_X]/1 mL
INACTIVE INGREDIENTS: ALCOHOL; WATER

D-72

NDC 58264-0072-1

INDICATIONS

PURPOSE

Supports pancreas function.

INGREDIENTS

ACTIVE

Apis mellifica 5x, Colocynthis 6x, Lycopodium clavatum 6x, Momordica balsamina 3x, Phosphorus 6x

INACTIVE

20% alcohol in purified water.

SUGGESTED DOSAGE

One dropper under tongue two times daily. Acute symptoms ½ dropper under tongue every 30 minutes for two hours.

STORAGE AND HANDLING

SHAKE WELL

Warnings

- Use only if cap seal is unbroken.

PREGNANCY OR BREAST FEEDING

- If pregnant or breastfeeding, ask a healthcare professional before use.

KEEP OUT OF REACH OF CHILDREN

- Keep this and all medication out of the reach of children.

To be used according to standard homeopathic indications.

PRINCIPAL DISPLAY PANEL - 1 FL. OZ. Bottle Label

DYNAMIC
NUTRITIONAL
ASSOCIATES, INC.

D 72

HOMEOPATHIC
STRESS FORMULA

1 FL. OZ.